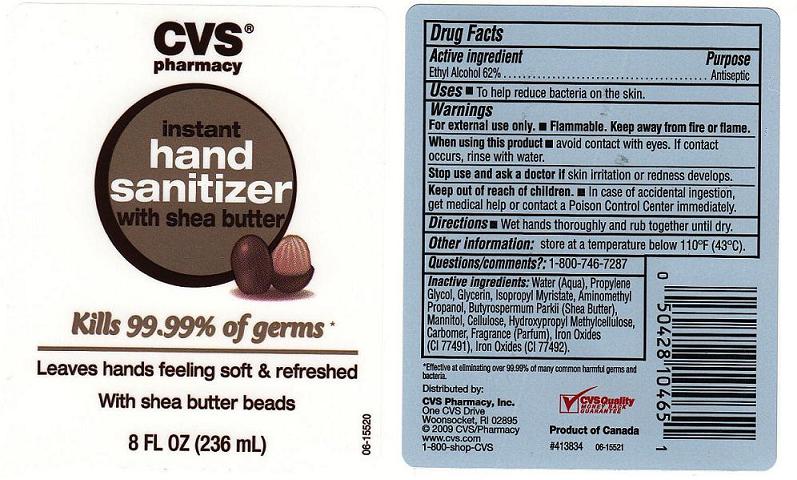 DRUG LABEL: Instant Hand Sanitizer 
NDC: 59779-224 | Form: GEL
Manufacturer: CVS Pharmacy
Category: otc | Type: HUMAN OTC DRUG LABEL
Date: 20100726

ACTIVE INGREDIENTS: ALCOHOL 62 mL/100 mL

Drug Facts Box - Back Label

Active Ingredient

Ethyl Alcohol 62%

Purpose

Antiseptic

Warnings

- For external use only.

- Flammable. Keep away from fire or flame.

When using this product

- avoid contact with eyes. If contact occurs, rinse with water.

Stop use and ask a doctor

- if skin irritation or redness develops.

Keep out of reach of children

- In case of accidental ingestion, get medical help or contact a Poison Control Center immediately.

Uses

To help reduce bacteria on the skin

Directions

Wet hands thoroughly and rub together until dry

Inactive Ingredints

Water (Aqua), Propylene Glycol, Glycerin, Isopropyl Myristate, Tocopheryl Acetate, Aminomethyl Propanol, Butyrospermum Parkii (Shea Butter), Mannitol, Cellulose, Hydroxypropyl Methylcellulose, Carbomer, Fragrance (Parfum), Iron Oxides (CI 77491), Iron Oxides (CI 77492).

Package Front and Back Labels

8OZ Front and Back Labels: cvs8.jpg